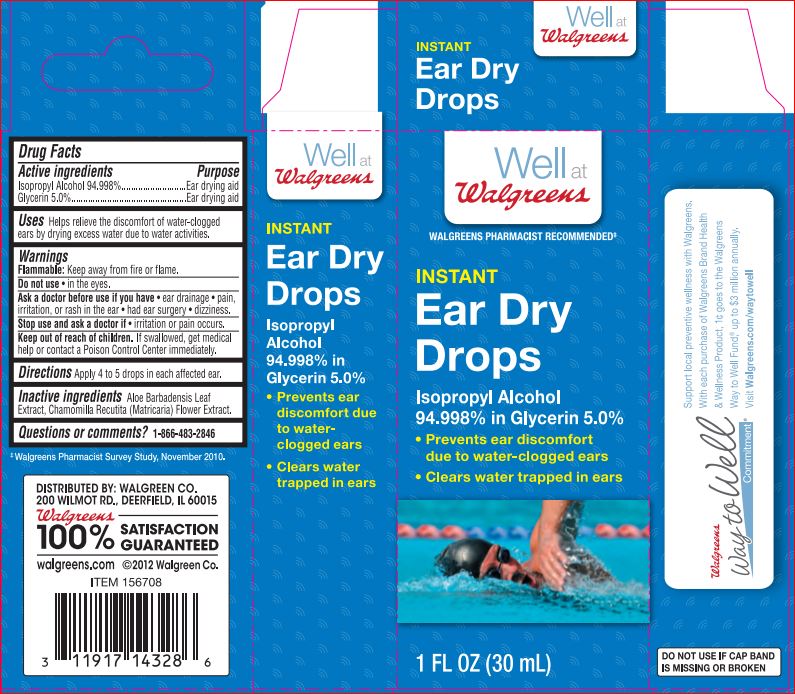 DRUG LABEL: EAR DRY DROPS
NDC: 0363-3019 | Form: LIQUID
Manufacturer: Walgreens
Category: otc | Type: HUMAN OTC DRUG LABEL
Date: 20180130

ACTIVE INGREDIENTS: Isopropyl Alcohol 94.998 1/100 mL
INACTIVE INGREDIENTS: ALOE VERA LEAF; CHAMOMILE; Glycerin 5.0 g/100 mL

WELL AT WALGREENS EAR DRY DROPS

Active ingredients

Isopropyl Alcohol 94.998%

Glycerin 5.0%

Purpose

Helps dry and relieve water-clogged ears

Uses

Helps relieve the discomfort of water-clogged ears by drying excess water due to water activities.

Warnings

Flammable: Keep away from fire or flame

Ask doctor before use if you have

- ear drainage
- pain, irritation, or rash in the ear
- dizziness

Stop use and ask a doctor if

- irritation or pain occurs

Keep out of reach of the children

If swallowed, get medical help or contact a Poison Control Center right away

Directions

Apply 4 to 5 drops in each affected ear

Inactive ingredient

Aloe Barbadensis Leaf Extract, Chamomilla Recutita (Matricaria) Flower Extract